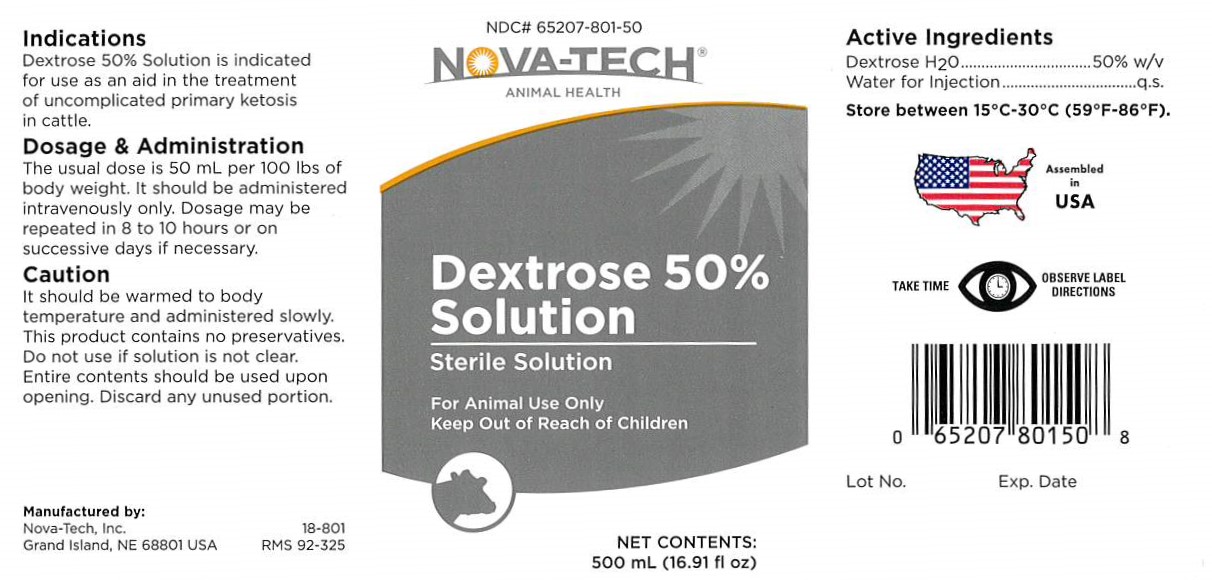 DRUG LABEL: Dextrose 50% Solution
NDC: 65207-801 | Form: INJECTION, SOLUTION
Manufacturer: Nova-Tech, Inc.
Category: animal | Type: OTC ANIMAL DRUG LABEL
Date: 20200313

ACTIVE INGREDIENTS: DEXTROSE MONOHYDRATE 50 g/100 mL

Dextrose 50% Solution

Dosage And Administration:

The usual dose is 50 mL per 100 lbs of body weight. It should be administered intravenously only. Dosage may be repeated in 8 to 10 hours or on successive days if necessary.

Caution:

It should be warmed to body temperature and administered slowly. This product contains no presevatives. Do not use if solution is not clear. Entire contents should be used upon opening. Discard any unused portion.

GENERAL PRECAUTIONS

FOR ANIMAL USE ONLY
KEEP OUT OF REACH OF CHILDREN

Active Ingredients

Dextrose H2O...........................50% w/v

Water for Injection...................q.s.

Indications:

Dextrose 50% Solution is indicated for use as an aid in the treatment of uncomplicated primary ketosis in cattle.

STORAGE AND HANDLING

Store between 15°C-30°C (59°F-86°F).

GENERAL PRECAUTIONS

TAKE TIME OBSERVE LABEL DIRECTIONS

INFORMATION FOR OWNERS/CAREGIVERS

Manufactured by:

Nova-Tech, Inc.

Grand Island, NE 68801 USA

18-801

RMS 92-325

NDC# 65207-801-50

Nova-Tech® Animal Health

Dextrose 50% Solution

Sterile Solution

Net Contents:

500 mL (16.91 fl oz)

Assembled in USA

Lot No. Exp. Date